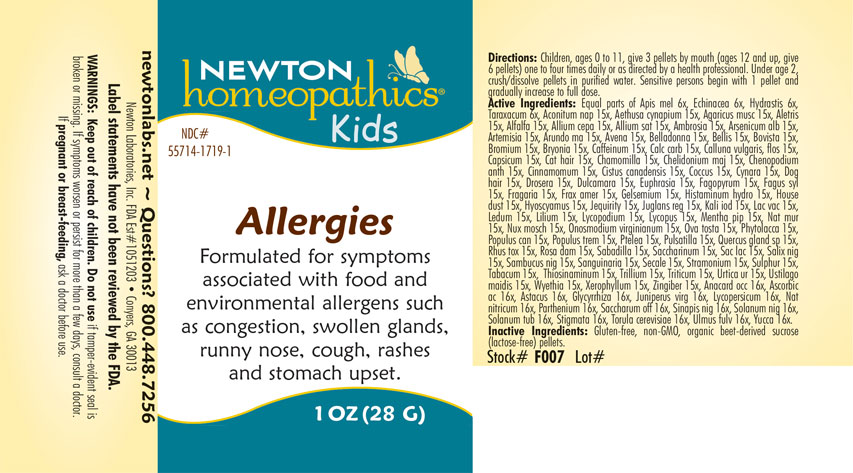 DRUG LABEL: Allergies
NDC: 55714-1719 | Form: PELLET
Manufacturer: Newton Laboratories, Inc.
Category: homeopathic | Type: HUMAN OTC DRUG LABEL
Date: 20240520

ACTIVE INGREDIENTS: PROTORTONIA CACTI 15 [hp_X]/1 g; CYNARA SCOLYMUS LEAF 15 [hp_X]/1 g; ONOSMODIUM VIRGINIANUM 15 [hp_X]/1 g; PHYTOLACCA AMERICANA ROOT 15 [hp_X]/1 g; YUCCA FILAMENTOSA 16 [hp_X]/1 g; SACCHARIN 15 [hp_X]/1 g; GINGER 15 [hp_X]/1 g; SODIUM CHLORIDE 15 [hp_X]/1 g; POPULUS TREMULOIDES LEAF 15 [hp_X]/1 g; SANGUINARIA CANADENSIS ROOT 15 [hp_X]/1 g; PARTHENIUM HYSTEROPHORUS 16 [hp_X]/1 g; CORN SILK 16 [hp_X]/1 g; SACCHAROMYCES CEREVISIAE 16 [hp_X]/1 g; ULMUS RUBRA BARK 16 [hp_X]/1 g; EGG SHELL, COOKED 15 [hp_X]/1 g; SCHOENOCAULON OFFICINALE SEED 15 [hp_X]/1 g; SAMBUCUS NIGRA FLOWERING TOP 15 [hp_X]/1 g; LYCOPUS VIRGINICUS 15 [hp_X]/1 g; LACTOSE, UNSPECIFIED FORM 15 [hp_X]/1 g; BLACK MUSTARD SEED 16 [hp_X]/1 g; CLAVICEPS PURPUREA SCLEROTIUM 15 [hp_X]/1 g; TRILLIUM ERECTUM ROOT 15 [hp_X]/1 g; ASCORBIC ACID 16 [hp_X]/1 g; ACONITUM NAPELLUS 15 [hp_X]/1 g; DATURA STRAMONIUM 15 [hp_X]/1 g; TOBACCO LEAF 15 [hp_X]/1 g; ALLYLTHIOUREA 15 [hp_X]/1 g; URTICA URENS 15 [hp_X]/1 g; ELYMUS REPENS ROOT 15 [hp_X]/1 g; USTILAGO MAYDIS 15 [hp_X]/1 g; WYETHIA HELENIOIDES ROOT 15 [hp_X]/1 g; XEROPHYLLUM ASPHODELOIDES 15 [hp_X]/1 g; APIS MELLIFERA 6 [hp_X]/1 g; TARAXACUM OFFICINALE 6 [hp_X]/1 g; AETHUSA CYNAPIUM 15 [hp_X]/1 g; AMANITA MUSCARIA FRUITING BODY 15 [hp_X]/1 g; ALETRIS FARINOSA ROOT 15 [hp_X]/1 g; ALFALFA 15 [hp_X]/1 g; ONION 15 [hp_X]/1 g; GARLIC 15 [hp_X]/1 g; AMBROSIA ARTEMISIIFOLIA 15 [hp_X]/1 g; ARSENIC TRIOXIDE 15 [hp_X]/1 g; ARTEMISIA VULGARIS ROOT 15 [hp_X]/1 g; ARUNDO PLINIANA ROOT 15 [hp_X]/1 g; AVENA SATIVA FLOWERING TOP 15 [hp_X]/1 g; ATROPA BELLADONNA 15 [hp_X]/1 g; BELLIS PERENNIS 15 [hp_X]/1 g; LYCOPERDON UTRIFORME FRUITING BODY 15 [hp_X]/1 g; BROMINE 15 [hp_X]/1 g; BRYONIA ALBA ROOT 15 [hp_X]/1 g; CAFFEINE 15 [hp_X]/1 g; OYSTER SHELL CALCIUM CARBONATE, CRUDE 15 [hp_X]/1 g; CALLUNA VULGARIS FLOWERING TOP 15 [hp_X]/1 g; CAPSICUM 15 [hp_X]/1 g; FELIS CATUS HAIR 15 [hp_X]/1 g; MATRICARIA CHAMOMILLA 15 [hp_X]/1 g; CHELIDONIUM MAJUS 15 [hp_X]/1 g; DYSPHANIA AMBROSIOIDES 15 [hp_X]/1 g; CINNAMON 15 [hp_X]/1 g; HELIANTHEMUM CANADENSE 15 [hp_X]/1 g; CANIS LUPUS FAMILIARIS HAIR 15 [hp_X]/1 g; DROSERA ANGLICA 15 [hp_X]/1 g; SOLANUM DULCAMARA TOP 15 [hp_X]/1 g; EUPHRASIA STRICTA 15 [hp_X]/1 g; FAGOPYRUM ESCULENTUM 15 [hp_X]/1 g; FAGUS SYLVATICA NUT 15 [hp_X]/1 g; ALPINE STRAWBERRY 15 [hp_X]/1 g; FRAXINUS AMERICANA BARK 15 [hp_X]/1 g; GELSEMIUM SEMPERVIRENS ROOT 15 [hp_X]/1 g; HISTAMINE DIHYDROCHLORIDE 15 [hp_X]/1 g; HOUSE DUST 15 [hp_X]/1 g; HYOSCYAMUS NIGER 15 [hp_X]/1 g; ABRUS PRECATORIUS SEED 15 [hp_X]/1 g; JUGLANS REGIA LEAF 15 [hp_X]/1 g; POTASSIUM IODIDE 15 [hp_X]/1 g; COW MILK 15 [hp_X]/1 g; RHODODENDRON TOMENTOSUM LEAFY TWIG 15 [hp_X]/1 g; LILIUM LANCIFOLIUM WHOLE FLOWERING 15 [hp_X]/1 g; TOXICODENDRON PUBESCENS LEAF 15 [hp_X]/1 g; LYCOPODIUM CLAVATUM SPORE 15 [hp_X]/1 g; ECHINACEA, UNSPECIFIED 6 [hp_X]/1 g; GOLDENSEAL 6 [hp_X]/1 g; SODIUM NITRATE 16 [hp_X]/1 g; SALIX NIGRA BARK 15 [hp_X]/1 g; SULFUR 15 [hp_X]/1 g; POPULUS BALSAMIFERA LEAF BUD 15 [hp_X]/1 g; QUERCUS ROBUR NUT 15 [hp_X]/1 g; MENTHA PIPERITA 15 [hp_X]/1 g; NUTMEG 15 [hp_X]/1 g; SOLANUM LYCOPERSICUM 16 [hp_X]/1 g; ANACARDIUM OCCIDENTALE FRUIT 16 [hp_X]/1 g; PTELEA TRIFOLIATA BARK 15 [hp_X]/1 g; ANEMONE PULSATILLA 15 [hp_X]/1 g; ROSA X DAMASCENA FLOWERING TOP 15 [hp_X]/1 g; ASTACUS ASTACUS 16 [hp_X]/1 g; GLYCYRRHIZA GLABRA 16 [hp_X]/1 g; JUNIPERUS VIRGINIANA TWIG 16 [hp_X]/1 g; SUCROSE 16 [hp_X]/1 g; SOLANUM NIGRUM WHOLE 16 [hp_X]/1 g; SOLANUM TUBEROSUM 16 [hp_X]/1 g
INACTIVE INGREDIENTS: SUCROSE CARAMEL

Allergies 1719P

INDICATIONS & USAGE SECTION

Formulated for symptoms associated with food and environmental allergens such as congestion, swollen glands, runny nose, cough, rashes and stomach upset.

DOSAGE & ADMINISTRATION SECTION

Directions: Children, ages 0 to 11, give 3 pellets by mouth (ages 12 and up take 6 pellets) as needed or directed by a health professional. Under age 2, crush/dissolve pellets in purified water. Sensitive persons begin with 1 pellet and gradually increase to full dose.

OTC - ACTIVE INGREDIENT SECTION

Equal parts of Apis mellifica 6x, Echinacea 6x, Hydrastis canadensis 6x, Taraxacum officinale 6x, Aconitum napellus 15x, Aethusa cynapium 15x, Agaricus muscarius 15x, Aletris farinosa 15x, Alfalfa 15x, Allium cepa 15x, Allium sativum 15x, Ambrosia artemisiaefolia 15x, Arsenicum album 15x, Artemisia vulgaris 15x, Arundo mauritanica 15x, Avena sativa 15x, Belladonna 15x, Bellis perrenis 15x, Bovista 15x, Bromium 15x, Bryonia 15x, Caffeinum 15x, Calcarea carbonica 15x, Calluna vulgaris, flos 15x, Capsicum annuum 15x, Cat hair 15x, Chamomilla 15x, Chelidonium majus 15x, Chenopodium anthelminticum 15x, Cinnamomum 15x, Cistus canadensis 15x, Coccus cacti 15x, Cynara scolymus 15x, Dog hair 15x, Drosera 15x, Dulcamara 15x, Euphrasia officinalis 15x, Fagopyrum esculentum 15x, Fagus sylvatica 15x, Fragaria vesca 15x, Fraxinis americana 15x, Gelsemium sempervirens 15x, Histaminum hydrochloricum 15x, House dust 15x, Hyoscyamus niger 15x, Jequirity 15x, Juglans regia 15x, Kali iodatum 15x, Lac vaccinum 15x, Ledum palustre 15x, Lilium tigrinum 15x, Lycopodium clavatum 15x, Lycopus virginicus 15x, Mentha piperita 15x, Natrum muriaticum 15x, Nux moschata 15x, Onosmodium virginianum 15x, Ova tosta 15x, Phytolacca decandra 15x, Populus candicans 15x, Populus tremuloides 15x, Ptelea trifoliata 15x, Pulsatilla 15x, Quercus glandium spiritus 15x, Rhus toxicodendron 15x, Rosa damascena 15x, Sabadilla 15x, Saccharinum 15x, Saccharum lactis 15x, Salix nigra 15x, Sambucus nigra 15x, Sanguinaria canadensis 15x, Secale cornutum 15x, Stramonium 15x, Sulphur 15x, Tabacum 15x, Thiosinaminum 15x, Trillium pendulum 15x, Triticum repens 15x, Urtica urens 15x, Ustilago maidis 15x, Wyethia helenoides 15x, Xerophyllum asphodeloides 15x, Zingiber officinale 15x, Anacardium occidentale 16x, Ascorbicum acidum 16x, Astacus fluviatilis 16x, Glycyrrhiza glabra 16x, Juniperus virginiana 16x, Lycopersicum esculentum 16x, Natrum nitricum 16x, Parthenium 16x, Saccharum officinale 16x, Sinapis nigra 16x, Solanum nigrum 16x, Solanum tuberosum 16x, Stigmata maidis 16x, Torula cerevisiae 16x, Ulmus fulva 16x, Yucca filamentosa 16x.

OTC - PURPOSE SECTION

Formulated for symptoms associated with food and environmental allergens such as congestion, swollen glands, runny nose, cough, rashes and stomach upset.

INACTIVE INGREDIENT SECTION

Inactive Ingredients: Gluten-free, non-GMO, organic beet-derived (lactose-free) pellets.

QUESTIONS SECTION

newtonlabs.net - Questions? 800.448.7256

Newton Laboratories, Inc. FDA Est # 1051203 Conyers, GA 30013

WARNINGS SECTION

WARNINGS: Keep out of reach of children. Do not use if tamper-evident seal is broken or missing. If symptoms worsen or persist for more than a few days, consult a doctor. If pregnant or breast-feeding, ask a doctor before use.

OTC - PREGNANCY OR BREAST FEEDING SECTION

If pregnant or breast-feeding, ask a doctor before use.

OTC - KEEP OUT OF REACH OF CHILDREN SECTION

Keep out of reach of children.